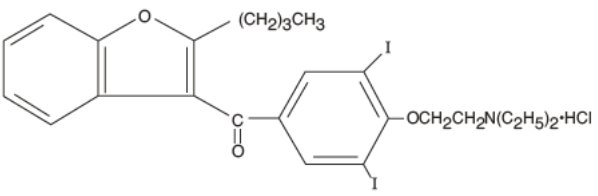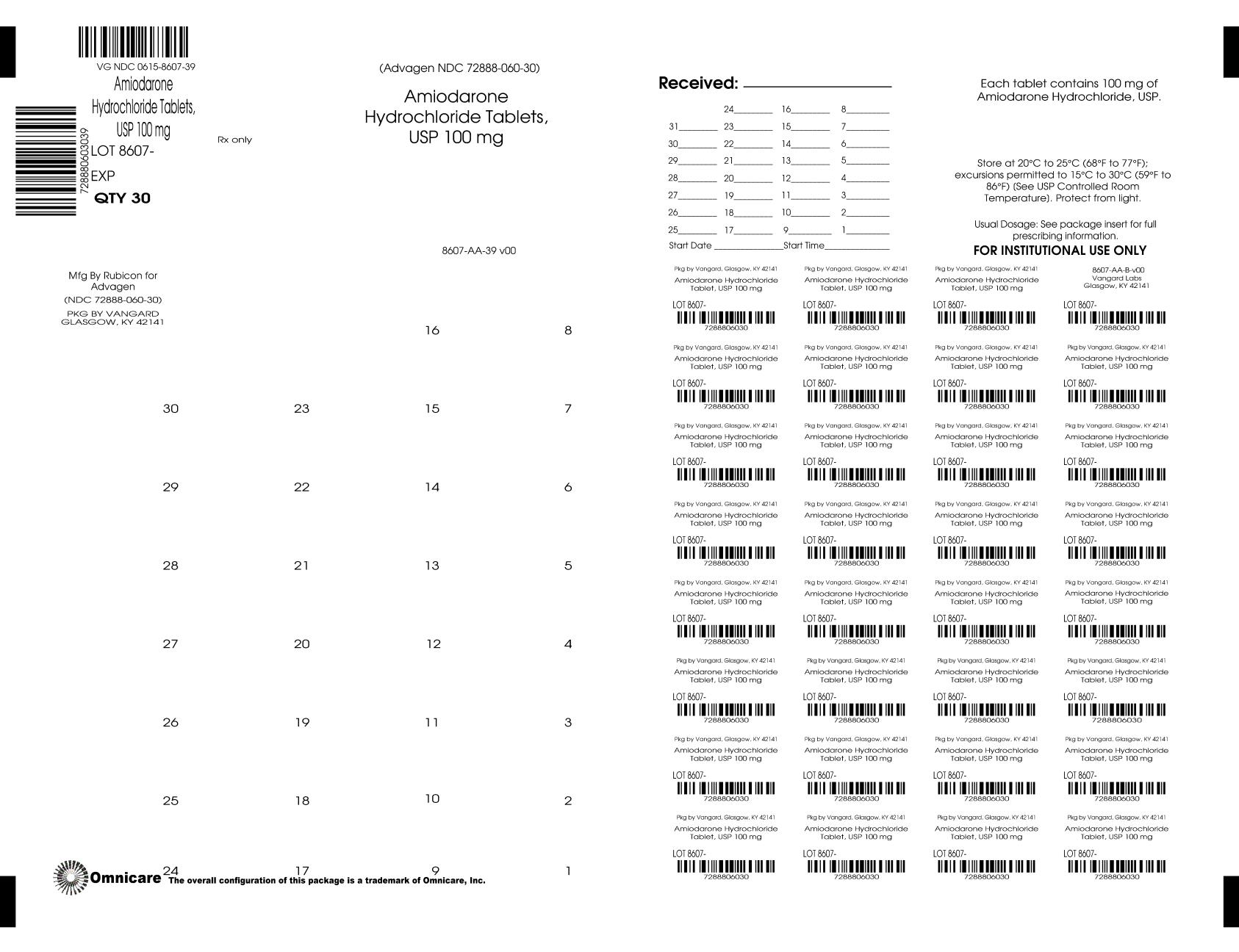 DRUG LABEL: Amiodarone Hydrochloride
NDC: 0615-8607 | Form: TABLET
Manufacturer: NCS HealthCare of KY, LLC dba Vangard Labs
Category: prescription | Type: HUMAN PRESCRIPTION DRUG LABEL
Date: 20251222

ACTIVE INGREDIENTS: AMIODARONE HYDROCHLORIDE 100 mg/1 1
INACTIVE INGREDIENTS: SILICON DIOXIDE; CROSCARMELLOSE SODIUM; CROSPOVIDONE; FD&C RED NO. 40; MAGNESIUM STEARATE

HIGHLIGHTS OF PRESCRIBING INFORMATION

These highlights do not include all the information needed to use Amiodarone Hydrochloride Tablets safely and effectively. See full prescribing information for Amiodarone Hydrochloride Tablets.
Amiodarone Hydrochloride Tablets, for oral use
Initial U.S. Approval: 1985

WARNING: PULMONARY, HEPATIC and CARDIAC TOXICITY

See full prescribing information for complete boxed warning.

- Reserve Amiodarone Hydrochloride Tablets for patients with the indicated life-threatening arrhythmias because its use is accompanied by substantial toxicity, some also life-threatening. Utilize alternative agents first. (1)
- Amiodarone Hydrochloride Tablet’s life-threatening toxicities include pulmonary (5.2), hepatic (5.3), and proarrhythmic (5.4).
- Initiate under hospital or specialist supervision. (5)

1 INDICATIONS AND USAGE

Amiodarone Hydrochloride Tablets is an antiarrhythmic indicated for:

- Recurrent ventricular fibrillation. (1)
- Recurrent hemodynamically unstable ventricular tachycardia. (1)

2 DOSAGE AND ADMINISTRATION

Initiate treatment with a loading doses of 800 to 1600 mg/day until initial therapeutic response occurs (usually 1 to 3 weeks). Once adequate arrhythmia control is achieved, or if side effects become prominent, reduce Amiodarone Hydrochloride Tablets dose to 600 to 800 mg/day for one month and then to the maintenance dose, usually 400 mg/day. (2)

3 DOSAGE FORMS AND STRENGTHS

Tablets, 100 mg, 200 mg, 400 mg. (3)

4 CONTRAINDICATIONS

Amiodarone Hydrochloride Tablets is contraindicated in patients with (4):

- Cardiogenic shock.
- Sick sinus syndrome, second- or third-degree AV block, bradycardia leading to syncope without a functioning pacemaker.
- Known hypersensitivity to the drug or any of its components.

5 WARNINGS AND PRECAUTIONS

- Persistence of Adverse Effects: Adverse reactions and drug interaction can persist for several weeks following discontinuation. (5.1)
- Impaired Vision: Corneal microdeposits (common; reversible), optic neuropathy/neuritis (rare; may lead to blindness). (5.5)
- Thyroid Abnormalities: Hyperthyroidism or hypothyroidism. (5.6)

6 ADVERSE REACTIONS

- The most common reactions (>1%) leading to discontinuation of Amiodarone Hydrochloride Tablets include pulmonary toxicity, paroxysmal ventricular tachycardia, congestive heart failure, and elevation of liver enzymes. (6)

To report SUSPECTED ADVERSE REACTIONS, contact Advagen Pharma Ltd. at 866-488-0312 or FDA at 1-800-FDA-1088 or www.fda.gov/medwatch.

7 DRUG INTERACTIONS

- Avoid coadministration of amiodarone with other antiarrhythmics and drugs known to prolong the QT interval. (7)
- Amiodarone is a substrate for CYP3A and CYP2C8, so inhibitors and inducers affect amiodarone exposure. (7)
- Amiodarone inhibits P-glycoprotein and CYP1A2, CYP2C9, CYP2D6, and CYP3A, increasing exposure to other drugs. (7)

8 USE IN SPECIFIC POPULATIONS

- Pregnancy: May cause fetal harm. (8.1)
- Lactation: Breastfeeding not recommended. (8.2)

FULL PRESCRIBING INFORMATION

WARNING: PULMONARY, HEPATIC and CARDIAC TOXICITY

Amiodarone Hydrochloride Tablets is intended for use only in patients with the indicated life-threatening arrhythmias because its use is accompanied by substantial toxicity [see Indications and Usage (1)].

Amiodarone Hydrochloride Tablets can cause pulmonary toxicity (hypersensitivity pneumonitis or interstitial/alveolar pneumonitis) that has resulted in clinically manifest disease at rates as high as 17% in some series of patients. Pulmonary toxicity has been fatal about 10% of the time. Obtain a baseline chest X-ray and pulmonary-function tests, including diffusion capacity, when Amiodarone Hydrochloride Tablets therapy is initiated. Repeat history, physical exam, and chest X-ray every 3 to 6 months [see Warnings and Precautions 5.2)].

Amiodarone Hydrochloride Tablets can cause hepatoxicity, which can be fatal. Obtain baseline and periodic liver transaminases and discontinue or reduce dose if the increase exceeds three times normal, or doubles in a patient with an elevated baseline. Discontinue Amiodarone Hydrochloride Tablets if the patient experiences signs or symptoms of clinical liver injury [see Warnings and Precautions (5.3)].

Amiodarone Hydrochloride Tablets can exacerbate arrhythmias. Initiate Amiodarone Hydrochloride Tablets in a clinical setting where continuous electrocardiograms and cardiac resuscitation are available [see Warnings and Precautions (5.4)].

1 INDICATIONS AND USAGE

Amiodarone Hydrochloride Tablets is indicated for the treatment of documented, life-threatening recurrent ventricular fibrillation and life-threatening recurrent hemodynamically unstable tachycardia in adults who have not responded to adequate doses of other available antiarrhythmics or when alternative agents cannot be tolerated.

2 DOSAGE AND ADMINISTRATION

Dosage must be individualized based on severity of arrhythmia and response. Use the lowest effective dose. Obtain baseline chest x-ray, pulmonary function tests, thyroid function tests, and liver aminotransferases. Correct hypokalemia, hypomagnesemia, and hypocalcemia before initiating treatment

Recommended Dosage:

Initiate treatment with a loading doses of 800 to 1600 mg/day until initial therapeutic response occurs (usually 1 to 3 weeks). Once adequate arrhythmia control is achieved, or if side effects become prominent, reduce Amiodarone Hydrochloride Tablets dose to 600 to 800 mg/day for one month and then to the maintenance dose, usually 400 mg/day.

Administration:

Administer Amiodarone Hydrochloride Tablets consistently with regard to meals [see Clinical Pharmacology (12.3)] . Administration of Amiodarone Hydrochloride Tablets in divided doses with meals is suggested for total daily doses of 1000 mg or higher, or when gastrointestinal intolerance occurs.

3 DOSAGE FORMS AND STRENGTHS

100 mg tablets: Mottled pink, round, flat-faced, bevelled-edge tablets, engraved “^
53” on one side and plain on other side.
200 mg tablets: Mottled pink, round, flat-faced, bevelled-edge tablets, engraved ‘^’ over score and ‘54’ below score on one side and plain on other side
400 mg tablets: Mottled pink, round, flat-faced bevelled-edge tablets, engraved “^” over score and “055” below score on one side and plain on the other side.

4 CONTRAINDICATIONS

- Cardiogenic shock.
- Sick sinus syndrome, second- or third-degree atrioventricular block, bradycardia leading to syncope without a functioning pacemaker.
- Known hypersensitivity to the drug or to any of its components, including iodine.

5 WARNINGS AND PRECAUTIONS

5.1 Persistence of Adverse Effects

Because of the long half-life of amiodarone (15 to 142 days) and its active metabolite desethylamiodarone (14 to 75 days), adverse reactions and drug interactions can persist for several weeks following amiodarone discontinuation [see Clinical Pharmacology (12.3)].

5.2 Pulmonary Toxicity

Amiodarone Hydrochloride Tablets may cause a clinical syndrome of cough and progressive dyspnea accompanied by functional, radiographic, gallium-scan, and pathological data consistent with pulmonary toxicity. Pulmonary toxicity secondary to Amiodarone Hydrochloride Tablets may result from either indirect or direct toxicity as represented by hypersensitivity pneumonitis (including eosinophilic pneumonia) or interstitial/alveolar pneumonitis, respectively. Rates of pulmonary toxicity have been reported to be as high as 17% and is fatal in about 10% of cases. Obtain a baseline chest X-ray and pulmonary-function tests, including diffusion capacity, when Amiodarone Hydrochloride Tablets therapy is initiated. Repeat history, physical exam, and chest X-ray every 3 to 6 months or if symptoms occur. Consider alternative antiarrhythmic therapy if the patient experiences signs or symptoms of pulmonary toxicity. Prednisone 40 to 60 mg/day tapered over several weeks may be helpful in treating pulmonary toxicity.

Adult Respiratory Distress Syndrome (ARDS)

Postoperatively, occurrences of ARDS have been reported in patients receiving Amiodarone Hydrochloride Tablets therapy who have undergone either cardiac or noncardiac surgery. Although patients usually respond well to vigorous respiratory therapy, in rare instances the outcome has been fatal.

5.3 Hepatic Injury

Asymptomatic elevations of hepatic enzyme levels are seen frequently, but Amiodarone Hydrochloride Tablets can cause life-threatening hepatic injury. Histology has resembled that of alcoholic hepatitis or cirrhosis. Obtain baseline and periodic liver transaminases. If transaminases exceed three times normal, or doubles in a patient with an elevated baseline, discontinue or reduce dose of Amiodarone Hydrochloride Tablets, obtain follow-up tests and treat appropriately.

5.4 Worsened Arrhythmia

Amiodarone Hydrochloride Tablets can exacerbate the presenting arrhythmia in about 2 to 5% of patients or cause new ventricular fibrillation, incessant ventricular tachycardia, increased resistance to cardioversion, and polymorphic ventricular tachycardia associated with QTc prolongation (Torsade de Pointes [TdP]).

Correct hypokalemia, hypomagnesemia, and hypocalcemia before initiating treatment with Amiodarone Hydrochloride Tablets, as these disorders can exaggerate the degree of QTc prolongation and increase the potential for TdP. Give special attention to electrolyte and acid-base balance in patients experiencing severe or prolonged diarrhea or receiving drugs affecting electrolyte levels, such as diuretics, laxatives, systemic corticosteroids, or amphotericin B.

5.5 Visual Impairment and Loss of Vision

Optic Neuropathy and Optic Neuritis

Cases of optic neuropathy and optic neuritis, usually resulting in visual impairment and sometimes permanent blindness, have been reported in patients treated with amiodarone and may occur at any time during therapy. If symptoms of visual impairment appear, such as changes in visual acuity and decreases in peripheral vision, consider discontinuing Amiodarone Hydrochloride Tablets and promptly refer for ophthalmic examination. Regular ophthalmic examination, including funduscopy and slit-lamp examination, is recommended during administration of Amiodarone Hydrochloride Tablets [see Adverse Reactions (6.1)] .

Corneal Microdeposits

Corneal microdeposits appear in the majority of adults treated with Amiodarone Hydrochloride Tablets. They are usually discernible only by slit-lamp examination, but give rise to symptoms such as visual halos or blurred vision in as many as 10% of patients. Corneal microdeposits are reversible upon reduction of dose or termination of treatment. Asymptomatic microdeposits alone are not a reason to reduce dose or discontinue treatment [see Adverse Reactions (6.1)] .

5.6 Thyroid Abnormalities

Amiodarone Hydrochloride Tablets inhibits peripheral conversion of thyroxine (T4) to triiodothyronine (T3) and may cause increased thyroxine levels, decreased T3levels, and increased levels of inactive reverse T3(rT3) in clinically euthyroid patients. Amiodarone Hydrochloride Tablets can cause either hypothyroidism (reported in up to 10% of patients) or hyperthyroidism (occurring in about 2% of patients). Monitor thyroid function prior to treatment and periodically thereafter, particularly in elderly patients, and in any patient with a history of thyroid nodules, goiter, or other thyroid dysfunction.

Hyperthyroidism mayinduce arrhythmia breakthrough. If any new signs of arrhythmia appear, the possibility of hyperthyroidism should be considered. Antithyroid drugs, β-adrenergic blockers, temporary corticosteroid therapy may be necessary to treat the symptoms of hyperthyroidism. The action of antithyroid drugs may be delayed in amiodarone-induced thyrotoxicosis because of substantial quantities of preformed thyroid hormones stored in the gland. Radioactive iodine therapy is contraindicated because of the low radioiodine uptake associated with amiodarone-induced hyperthyroidism. Amiodarone Hydrochloride Tablets-induced hyperthyroidism may be followed by a transient period of hypothyroidism.

Hypothyrodism may be primary or subsequent to resolution of preceding amiodarone-induced hyperthyroidism. Severe hypothyroidism and myxedema coma, sometimes fatal, have been reported in association with amiodarone therapy. In some clinically hypothyroid amiodarone-treated patients, free thyroxine index values may be normal. Manage hypothyroidism by reducing the dose of or discontinuing Amiodarone Hydrochloride Tablets and thyroid hormone supplementation.

5.7 Bradycardia

Amiodarone Hydrochloride Tablets causes symptomatic bradycardia or sinus arrest with suppression of escape foci in 2 to 4% of patients. The risk is increased by electrolytic disorders or use of concomitant antiarrhythmics or negative chronotropes [see Drug Interactions (7)]. Bradycardia may require a pacemaker for rate control.

Postmarketing cases of symptomatic bradycardia, some requiring pacemaker insertion and at least one fatal, have been reported when ledipasvir/sofosbuvir or sofosbuvir with simeprevir were initiated in patients on amiodarone. Bradycardia generally occurred within hours to days, but in some cases presented up to 2 weeks after initiating antiviral treatment. Bradycardia generally resolved after discontinuation of antiviral treatment. The mechanism for this effect is unknown. Monitor heart rate in patients taking or recently discontinuing amiodarone when starting antiviral treatment [see Drug Interactions (7)] .

5.8 Implantable Cardiac Devices

In patients with implanted defibrillators or pacemakers, chronic administration of antiarrhythmic drugs may affect pacing or defibrillation thresholds. Therefore, at the inception of and during amiodarone treatment, pacing and defibrillation thresholds should be assessed.

5.9 Fetal Toxicity

Amiodarone Hydrochloride Tablets may cause fetal harm when administered to a pregnant woman. Fetal exposure may increase the potential for cardiac, thyroid, neurodevelopmental, neurological, and growth effects in neonate [see Use in Specific Populations (8.1)] .

5.10 Peripheral Neuropathy

Chronic administration of Amiodarone Hydrochloride Tablets may lead to peripheral neuropathy, which may not resolve when Amiodarone Hydrochloride Tablets is discontinued.

5.11 Photosensitivity and Skin Discoloration

Amiodarone Hydrochloride Tablets induces photosensitization in about 10% of patients; some protection may be afforded sun-barrier creams or protective clothing. During long-term treatment, a blue-gray discoloration of the exposed skin may occur. The risk may be increased in patients of fair complexion or those with excessive sun exposure. Some reversal of discoloration may occur upon drug discontinuation.

5.12 Surgery

Volatile Anesthetic Agents

Patients on Amiodarone Hydrochloride Tablets therapy may be more sensitive to the myocardial depressant and conduction effects of halogenated inhalational anesthetics.

6 ADVERSE REACTIONS

The following serious adverse reactions are described in more detail in other sections of the prescribing information:

- Pulmonary Toxicity [see Warnings and Precautions (5.2)]
- Hepatic Injury [see Warnings and Precautions (5.3)]
- Worsened Arrhythmia [see Warnings and Precautions (5.4)]
- Visual Impairment and Loss of Vision [see Warnings and Precautions (5.5)]
- Thyroid Abnormalities [see Warnings and Precautions (5.6)]
- Bradycardia [see Warnings and Precautions (5.7)]
- Peripheral Neuropathy [see Warnings and Precautions (5.10)]
- Photosensitivity and Skin Discoloration [see Warnings and Precautions (5.11)]

6.1 Clinical Trials Experience

Because clinical trials are conducted under widely varying conditions, adverse reaction rates observed in the clinical trials of a drug cannot be directly compared to rates in the clinical trials of another drug and may not reflect the rates observed in practice.

At the usual maintenance dose (400 mg/day) and above, Amiodarone Hydrochloride Tablets causes adverse reactions in about three-fourths of all patients, resulting in discontinuation in 7 to 18%.

In surveys of almost 5,000 patients treated in open U.S. studies and in published reports of treatment with Amiodarone Hydrochloride Tablets, the adverse reactions most frequently requiring discontinuation of Amiodarone Hydrochloride Tablets included pulmonary infiltrates or fibrosis, paroxysmal ventricular tachycardia, congestive heart failure, and elevation of liver enzymes. Other symptoms causing discontinuations less often included visual disturbances, photosensitivity, blue skin discoloration, hyperthyroidism, and hypothyroidism.

The following side-effect rates are based on a retrospective study of 241 patients treated for 2 to 1,515 days (mean 441.3 days):

Thyroid

Common: Hypothyroidism, hyperthyroidism.

Cardiovascular

Common: Congestive heart failure, cardiac arrhythmias, SA node dysfunction.

Gastrointestinal

Very common: Nausea, vomiting.

Common: Constipation, anorexia, abdominal pain.

Dermatologic

Common: Solar dermatitis/photosensitivity.

Neurologic

Common: Malaise and fatigue, tremor/abnormal involuntary movements, lack of coordination, abnormal gait/ataxia, dizziness, paresthesias, decreased libido, insomnia, headache, sleep disturbances.

Ophthalmic

Common: Visual disturbances.

Hepatic

Common: Abnormal liver-function tests, nonspecific hepatic disorders.

Respiratory

Common: Pulmonary inflammation or fibrosis.

Other

Common: Flushing, abnormal taste and smell, edema, abnormal salivation, coagulation abnormalities.

Uncommon: Blue skin discoloration, rash, spontaneous ecchymosis, alopecia, hypotension, and cardiac conduction abnormalities.

6.2 Postmarketing Experience

The following adverse reactions have been identified during post-approval use of Amiodarone Hydrochloride Tablets. Because these reactions are reported voluntarily from a population of uncertain size, it is not always possible to reliably estimate their frequency or establish a causal relationship to drug exposure.

Hematologic:Hemolytic anemia, aplastic anemia, pancytopenia, neutropenia, thrombocytopenia, agranulocytosis, granuloma.

Immune:anaphylactic/anaphylactoid reaction (including shock), angioedema.

Neurologic:pseudotumor cerebri, parkinsonian symptoms such as akinesia and bradykinesia (sometimes reversible with discontinuation of therapy), demyelinating polyneuropathy.

Psychiatric:hallucination, confusional state, disorientation, delirium.

Cardiac:hypotension (sometimes fatal), sinus arrest.

Respiratory:eosinophilic pneumonia, acute respiratory distress syndrome in the post-operative setting, bronchospasm, bronchiolitis obliterans organizing pneumonia, pulmonary alveolar hemorrhage, pleural effusion, pleuritis.

Gastrointestinal:pancreatitis, acute pancreatitis.

Hepatic:hepatitis, cholestatic hepatitis, cirrhosis.

Skin and Subcutaneous Tissue Disorders:urticaria, toxic epidermal necrolysis (sometimes fatal), erythema multiforme, stevens-Johnson syndrome, exfoliative dermatitis, bullous dermatitis, drug rash with eosinophilia and systemic symptoms (DRESS), eczema, pruritus, skin cancer, lupus-like syndrome.

Musculoskeletal:myopathy, muscle weakness, rhabdomyolysis.

Renal:renal impairment, renal insufficiency, acute renal failure.

Reproductive:epididymitis, impotence.

Body as a whole:fever, dry mouth.

Endocrine and metabolic:thyroid nodules/ thyroid cancer, syndrome of inappropriate antidiuretic hormone secretion (SIADH).

Vascular:vasculitis.

7 DRUG INTERACTIONS

Because of amiodarone’s long half-life, expect drug interactions to persist for weeks to months after discontinuation of amiodarone. Drug interactions with amiodarone are described in Table 1 below.

Table 1: Amiodarone Drug Interactions
Concomitant Drug; Class/Name | Examples | Clinical Comment
Pharmacodynamic Interactions
QT Prolonging Drugs | class I and III antiarrhythmics, lithium, certain phenothiazines, tricyclic antidepressants, certain fluoroquinolone and macrolide antibiotics, azole antifungals, halogenated inhalation anesthetic agents | Increased risk of Torsade de Pointes. Avoid concomitant use.
Negative Chronotropes | digoxin, beta blockers, verapamil, diltiazem, clonidine, ivabradine | Potentiates the electrophysiologic and hemodynamic effects of amiodarone, resulting in bradycardia, sinus arrest, and AV block. Monitor heart rate.
Pharmacokinetic Interactions
CYP450 Inhibitors | grapefruit juice, certain fluoroquinolone and macrolide antibiotics, azole antifungals, cimetidine, certain protease inhibitors | Increased exposure of amiodarone. Avoid concomitant use.
CYP450 Inducers | St. John’s Wort | Reduced amiodarone serum levels.
Cyclosporine |  | Increased plasma levels of cyclosporine have been reported resulting in elevated creatinine, despite reduction of cyclosporine dose. Monitor cyclosporine drug levels and renal function with concomitant use.
Cholestyramine |  | Reduced amiodarone serum levels.
Antiarrhythmics | quinidine, procainamide, flecainide | Reserve concomitant use for patients who are unresponsive to a single agent. Antiarrhythmic metabolism inhibited by amiodarone. Initiate antiarrhythmic at a lower than usual dose and monitor patient carefully. Reduce dose levels of previously administered antiarrhythmic by 30 to 50% for several days after transitioning to oral amiodarone. Evaluate continued need for antiarrhythmic.
Digoxin |  | Increased digoxin concentration. Reduce digoxin by half or discontinue. If continued, monitor for evidence of toxicity.
HMG-CoA Reductase Inhibitors | simvastatin, lovastatin, atorvastatin | Increased plasma concentration of HMG- CoA reductase inhibitor. Limit the dose of lovastatin to 40 mg. Limit the coadministered dose of simvastatin to 20 mg. Lower starting dose of other CYP3A4 substrates may be required.
Warfarin |  | Potentiates anticoagulant response and can result in serious or fatal bleeding. Coadministration increases prothrombin time by 100% after 3 to 4 days. Reduce warfarin dose by one-third to one-half and monitor prothrombin times.
Phenytoin |  | Increased steady-state levels of phenytoin. Monitor phenytoin levels.
Hepatitis C Direct Acting Antiviral | sofosbuvir | Cases of symptomatic bradyarrhythmia requiring pacemaker insertion have been reported in patients on oral maintenance amiodarone who initiated therapy with sofosbuvir.
CYP3A Substrate | lidocaine | Sinus bradycardia has been reported with oral amiodarone in combination with lidocaine given for local anesthesia. Monitor heart rate. A lower starting dose of lidocaine may be required.
CYP3A Substrate | fentanyl | Fentanyl in combination with amiodarone may cause hypotension, bradycardia, and decreased cardiac output.

8 USE IN SPECIFIC POPULATIONS

8.1 Pregnancy

Risk Summary

Available data from postmarketing reports and published case series indicate that amiodarone use in pregnant women may increase the risk for fetal adverse effects including neonatal hypo- and hyperthyroidism, neonatal bradycardia, neurodevelopmental abnormalities, preterm birth and fetal growth restriction. Amiodarone and its metabolite, desethylamiodarone (DEA), cross the placenta. Untreated underlying arrhythmias, including ventricular arrhythmias, during pregnancy pose a risk to the mother and fetus (see Clinical Considerations). In animal studies, administration of amiodarone to rabbits, rats, and mice during organogenesis resulted in embryo- fetal toxicity at doses less than the maximum recommended human maintenance dose (see Data) . Advise pregnant women of the potential risk to a fetus.

The estimated background risk of major birth defects and miscarriage for the indicated population is unknown. All pregnancies have a background risk of birth defect, loss or other adverse outcomes. In the U.S. general population, the estimated background risk of major birth defects and miscarriage in clinically recognized pregnancies is 2%-4% and 15%-20%, respectively.

Clinical Considerations

Disease-associated maternal and or embryo/fetal Risk

The incidence of ventricular tachycardia is increased and may be more symptomatic during pregnancy. Ventricular arrhythmias most often occur in pregnant women with underlying cardiomyopathy, congenital heart disease, valvular heart disease, or mitral valve prolapse. Most tachycardia episodes are initiated by ectopic beats and the occurrence of arrhythmia episodes may therefore, increase during pregnancy due to the increased propensity to ectopic activity. Breakthrough arrhythmias may also occur during pregnancy, as therapeutic treatment levels may be difficult to maintain due to the increased volume of distribution and increased drug metabolism inherent in the pregnant state.

Fetal/Neonatal adverse reactions

Amiodarone and its metabolite have been shown to cross the placenta. Adverse fetal effects associated with maternal amiodarone use during pregnancy may include neonatal bradycardia, QT prolongation, and periodic ventricular extrasystoles, neonatal hypothyroidism (with or without goiter) detected antenatally or in the newborn and reported even after a few days of exposure, neonatal hyperthyroxinemia, neurodevelopmental abnormalities independent of thyroid function, including speech delay and difficulties with written language and arithmetic, delayed motor development, and ataxia, jerk nystagmus with synchronous head titubation, fetal growth restriction, and premature birth. Monitor the newborn for signs and symptoms of thyroid disorder and cardiac arrhythmias.

Labor and Delivery

Risk of arrhythmias may increase during labor and delivery. Patients treated with Amiodarone Hydrochloride Tablets should be monitored continuously during labor and delivery [see Warnings and Precautions (5.4)].

Data

Animal Data

In pregnant rats and rabbits during the period of organogenesis, amiodarone HCl in doses of 25 mg/kg/day (approximately 0.4 and 0.9 times, respectively, the maximum recommended human maintenance dose*) had no adverse effects on the fetus. In the rabbit,
75 mg/kg/day (approximately 2.7 times the maximum recommended human maintenance dose*) caused abortions in greater than 90% of the animals. In the rat, doses of 50 mg/kg/day or more were associated with slight displacement of the testes and an increased incidence of incomplete ossification of some skull and digital bones; at 100 mg/kg/day or more, fetal body weights were reduced; at 200 mg/kg/day, there was an increased incidence of fetal resorption. (These doses in the rat are approximately 0.8, 1.6 and 3.2 times the maximum recommended human maintenance dose*) Adverse effects on fetal growth and survival also were noted in one of two strains of mice at a dose of 5 mg/kg/day (approximately 0.04 times the maximum recommended human maintenance dose*).

*600 mg in a 60 kg patient (doses compared on a body surface area basis)

8.2 Lactation

Risk Summary

Amiodarone and one of its major metabolites, DEA, are present in breastmilk at between 3.5% and 45% of the maternal weight- adjusted dosage of amiodarone. There are cases of hypothyroidism and bradycardia in breastfed infants, although it is unclear if these effects are due to amiodarone exposure in breastmilk. Breastfeeding is not recommended during treatment with Amiodarone Hydrochloride Tablets [see Warnings and Precautions (5.6, 5.7)] .

8.3 Females and Males of Reproductive Potential

Infertility

Based on animal fertility studies, Amiodarone Hydrochloride Tablets may reduce female and male fertility. It is not known if this effect is reversible. [see Nonclinical Toxicology (13.1)] .

8.4 Pediatric Use

The safety and effectiveness of Amiodarone Hydrochloride Tablets in pediatric patients have not been established.

8.5 Geriatric Use

Normal subjects over 65 years of age show lower clearances and increased drug half-life than younger subjects [see Clinical Pharmacology (12.3)]. In general, dose selection for an elderly patient should be cautious, usually starting at the low end of the dosing range, reflecting the greater frequency of decreased hepatic, renal, or cardiac function, and of concomitant disease or other drug therapy.

10 OVERDOSAGE

There have been cases, some fatal, of Amiodarone Hydrochloride Tablets overdose.

Monitor the patient’s cardiac rhythm and blood pressure, and, if bradycardia ensues, a β-adrenergic agonist or a pacemaker may be used. Treat hypotension with inadequate tissue perfusion with positive inotropic and vasopressor agents. Neither Amiodarone Hydrochloride Tablets nor its metabolite is dialyzable.

11 DESCRIPTION

Amiodarone Hydrochloride Tablets (amiodarone HCl) is an antiarrhythmic drug, available for oral administration as mottled pink, round, flat faced bevelled edge tablets containing 100 mg, 200 mg and 400 mg of amiodarone hydrochloride. The inactive ingredients present are colloidal silicon dioxide, croscarmellose sodium, crospovidone, FD&C Red #40 Al Lake and magnesium stearate. Amiodarone Hydrochloride Tablets is a benzofuran derivative: 2-butyl-3-benzofuranyl 4-[2-(diethylamino)-ethoxy]- 3,5-diiodophenyl ketone hydrochloride.

The structural formula is as follows:

C25H29I2NO3• HCl Molecular Weight: 681.8

Amiodarone HCl is a white to cream-colored crystalline powder. It is slightly soluble in water, soluble in alcohol, and freely soluble in chloroform. It contains 37.3% iodine by weight.

The Product meets USP Dissolution Test 2.

12 CLINICAL PHARMACOLOGY

12.1 Mechanism of Action

Amiodarone is considered a class III antiarrhythmic drug, but it possesses electrophysiologic characteristics of all four Vaughan Williams classes. Like class I drugs, amiodarone blocks sodium channels at rapid pacing frequencies, and like class II drugs, amiodarone exerts a noncompetitive antisympathetic action. One of its main effects, with prolonged administration, is to lengthen the cardiac action potential, a class III effect. The negative chronotropic effect of amiodarone in nodal tissues is similar to the effect of class IV drugs. In addition to blocking sodium channels, amiodarone blocks myocardial potassium channels, which contributes to slowing of conduction and prolongation of refractoriness. The antisympathetic action and the block of calcium and potassium channels are responsible for the negative dromotropic effects on the sinus node and for the slowing of conduction and prolongation of refractoriness in the atrioventricular (AV) node. Its vasodilatory action can decrease cardiac workload and consequently myocardial oxygen consumption.

Amiodarone Hydrochloride Tablets prolongs the duration of the action potential of all cardiac fibers while causing minimal reduction of dV/dt (maximal upstroke velocity of the action potential). The refractory period is prolonged in all cardiac tissues. Amiodarone Hydrochloride Tablets increases the cardiac refractory period without influencing resting membrane potential, except in automatic cells where the slope of the prepotential is reduced, generally reducing automaticity. These electrophysiologic effects are reflected in a decreased sinus rate of 15 to 20%, increased PR and QT intervals of about 10%, the development of U-waves, and changes in T-wave contour. These changes should not require discontinuation of Amiodarone Hydrochloride Tablets as they are evidence of its pharmacological action, although Amiodarone Hydrochloride Tablets can cause marked sinus bradycardia or sinus arrest and heart block [see Warnings and Precautions (5.4)] .

Hemodynamics

In animal studies and after intravenous administration in man, Amiodarone Hydrochloride Tablets relaxes vascular smooth muscle, reduces peripheral vascular resistance (afterload), and slightly increases cardiac index. After oral dosing, however, Amiodarone Hydrochloride Tablets produces no significant change in left ventricular ejection fraction (LVEF), even in patients with depressed LVEF. After acute intravenous dosing in man, Amiodarone Hydrochloride Tablets may have a mild negative inotropic effect.

12.2 Pharmacodynamics

There is no well-established relationship between plasma concentration and effectiveness, but it does appear that concentrations much below 1 mg/L are often ineffective and that levels above 2.5 mg/L are generally not needed. Plasma-concentration measurements can be used to identify patients whose levels are unusually low, and who might benefit from a dose increase, or unusually high, and who might have dosage reduction in the hope of minimizing side effects.

Effects on abnormal rhythms are not seen before 2 to 3 days and usually require 1 to 3 weeks, even when a loading dose is used. There may be a continued increase in effect for longer periods still. There is evidence that the time to effect is shorter when a loading-dose regimen is used.

Consistent with the slow rate of elimination, antiarrhythmic effects persist for weeks or months after Amiodarone Hydrochloride Tablets is discontinued, but the time of recurrence is variable and unpredictable. In general, when the drug is resumed after recurrence of the arrhythmia, control is established relatively rapidly compared to the initial response, presumably because tissue stores were not wholly depleted.

12.3 Pharmacokinetics

Absorption

Following oral administration in humans, Amiodarone Hydrochloride Tablets is slowly and variably absorbed. The bioavailability of Amiodarone Hydrochloride Tablets is approximately 50%. Maximum plasma concentrations are attained 3 to 7 hours after a single dose. Plasma concentrations with chronic dosing at 100 to 600 mg/day are approximately dose proportional, with a mean 0.5 mg/L increase for each 100 mg/day. These means, however, include considerable individual variability.

Food increases the rate and extent of absorption of Amiodarone Hydrochloride Tablets. The effects of food upon the bioavailability of Amiodarone Hydrochloride Tablets have been studied in 30 healthy subjects who received a single 600-mg dose immediately after consuming a high-fat meal and following an overnight fast. The area under the plasma concentration-time curve (AUC) and the peak plasma concentration (Cmax) of amiodarone increased by 2.3 (range 1.7 to 3.6) and 3.8 (range 2.7 to 4.4) times, respectively, in the presence of food. Food also increased the rate of absorption of amiodarone, decreasing the time to peak plasma concentration (Tmax) by 37%. The mean AUC and mean Cmaxof the major metabolite of amiodarone, DEA increased by 55% (range 58 to 101%) and 32% (range 4 to 84%), respectively, but there was no change in the Tmaxin the presence of food.

Distribution

Amiodarone Hydrochloride Tablets is highly protein-bound (approximately 96%). Amiodarone Hydrochloride Tablets has a very large but variable volume of distribution, averaging about 60 L/kg, because of extensive accumulation in various sites, especially adipose tissue and highly perfused organs, such as the liver, lung, and spleen.

One major metabolite of Amiodarone Hydrochloride, DEA, has been identified in man; it accumulates to an even greater extent in almost all tissues. No data are available on the activity of DEA in humans, but in animals, it has significant electrophysiologic and antiarrhythmic effects generally similar to amiodarone itself. DEA’s precise role and contribution to the antiarrhythmic activity of oral amiodarone are not certain. The development of maximal ventricular class III effects after oral Amiodarone Hydrochloride Tablets administration in humans correlates more closely with DEA accumulation over time than with amiodarone accumulation.

Elimination

Following single dose administration in 12 healthy subjects, Amiodarone Hydrochloride Tablets exhibited multi-compartmental pharmacokinetics with a mean apparent plasma terminal elimination half-life of 58 days (range 15 to 142 days) for amiodarone and 36 days (range 14 to 75 days) for the active metabolite (DEA). In patients, following discontinuation of chronic oral therapy, Amiodarone Hydrochloride Tabletshas been shown to have a biphasic elimination with an initial 50% reduction of plasma levels after 2.5 to 10 days. A much slower terminal plasma-elimination phase shows a half-life of the parent compound ranging from 26 to 107 days, with a mean of approximately 53 days and most patients in the 40- to 55-day range. In the absence of a loading-dose period, steady-state plasma concentrations, at constant oral dosing, would therefore be reached between 130 and 535 days, with an average of 265 days. For the metabolite, the mean plasma- elimination half-life was approximately 61 days. These data probably reflect an initial elimination of drug from well-perfused tissue (the 2.5- to 10-day half-life phase), followed by a terminal phase representing extremely slow elimination from poorly perfused tissue compartments such as fat.

The considerable inter-subject variation in both phases of elimination, as well as uncertainty as to what compartment is critical to drug effect, requires attention to individual responses once arrhythmia control is achieved with loading doses because the correct maintenance dose is determined, in part, by the elimination rates. Individualize maintenance doses of Amiodarone Hydrochloride Tablets [see Dosage and Administration (2)] .

Metabolism

Amiodarone is metabolized to DEA by the cytochrome P450 (CYP) enzyme group, specifically CYP3A and CYP2C8. The CYP3A isoenzyme is present in both the liver and intestines. In vitro, amiodarone and DEA exhibit a potential to inhibit CYP2C9, CYP2C19, CYP2D6, CYP3A, CYP2A6, CYP2B6 and CYP2C8. Amiodarone and DEA have also a potential to inhibit some transporters such as P-glycoprotein and organic cation transporter (OCT2).

Excretion

Amiodarone is eliminated primarily by hepatic metabolism and biliary excretion and there is negligible excretion of amiodarone or DEA in urine. Neither amiodarone nor DEA is dialyzable.

Specific Populations

Effect of Age:Normal subjects over 65 years of age show lower clearances (about 100 mL/hr/kg) than younger subjects (about 150 mL/hr/kg) and an increase in t½ from about 20 to 47 days.

Renal Impairment:Renal impairment does not influence the pharmacokinetics of amiodarone or DEA.

Hepatic Impairment:After a single dose of intravenous amiodarone to cirrhotic patients, significantly lower Cmaxand average concentration values are seen for DEA, but mean amiodarone levels are unchanged.

Cardiac Disease:In patients with severe left ventricular dysfunction, the pharmacokinetics of amiodarone are not significantly altered but the terminal elimination t½ of DEA is prolonged.

Although no dosage adjustment for patients with renal, hepatic, or cardiac abnormalities has been defined during chronic treatment with oral amiodarone, close clinical monitoring is prudent for elderly patients and those with severe left ventricular dysfunction.

Drug Interactions:

Effects of Other Agents on Amiodarone

Grapefruit juice:Grapefruit juice given to healthy volunteers increased amiodarone AUC by 50% and Cmaxby 84%, and decreased DEA to unquantifiable concentrations.

Cimetidineinhibits CYP3A and can increase serum amiodarone levels.

Cholestyraminereduces enterohepatic circulation of amiodarone thereby increasing its elimination. This results in reduced amiodarone serum levels and half-life.

Effects of Amiodarone on Agents:

CYP3A substrates:

Amiodarone taken concomitantly with quinidineincreases the quinidine serum concentration by 33% after two days. Amiodarone taken concomitantly with procainamidefor less than seven days increases plasma concentrations of procainamide and n-acetyl procainamide by 55% and 33%, respectively.

Loratadine,a non-sedating antihistaminic, is metabolized primarily by CYP3A and its metabolism can be inhibited by amiodarone.

Metabolism of lidocainecan be inhibited by amiodarone.

Cyclophosphamideis a prodrug, metabolized by CYP450 including CYP3A to an active metabolite. The metabolism of cyclophosphamide may be inhibited by amiodarone.

Clopidogrel,an inactive thienopyridine prodrug, is metabolized in the liver by CYP3A to an active metabolite. A potential interaction between clopidogrel and amiodarone resulting in ineffective inhibition of platelet aggregation has been reported.

Macrolide/ketolide antibiotics:

Amiodarone can inhibit the metabolism of macrolide/ketolide antibiotics(except for azithromycin) and systemic azole antifungal drugs.

P-glycoprotein substrates:

Amiodarone taken concomitantly with digoxinincreases the serum digoxin concentration by 70% after one day.

Dabigatran etexilatewhen taken concomitantly with oral amiodarone can result in elevated serum concentration of dabigatran.

Dextromethorphanis a substrate for both CYP2D6 and CYP3A. Amiodarone inhibits CYP2D6. Chronic (> 2 weeks) oral amiodarone administration impairs metabolism of dextromethorphan can lead to increased serum concentrations.

13 NONCLINICAL TOXICOLOGY

13.1 Carcinogenesis, Mutagenesis, Impairment of Fertility

Amiodarone HCl was associated with a statistically significant, dose-related increase in the incidence of thyroid tumors (follicular adenoma and/or carcinoma) in rats. The incidence of thyroid tumors was greater than control at the lowest dose level tested, i.e.,
5 mg/kg/day (approximately 0.08 times the maximum recommended human maintenance dose*). Mutagenicity studies (Ames, micronucleus, and lysogenic tests) with Amiodarone Hydrochloride Tablets were negative.

In a study in which amiodarone HCl was administered to male and female rats, beginning 9 weeks prior to mating, reduced fertility was observed at a dose level of 90 mg/kg/day (approximately 1.4 times the maximum recommended human maintenance dose*).

*600 mg in a 60 kg patient (dose compared on a body surface area basis)

16 HOW SUPPLIED/STORAGE AND HANDLING

Amiodarone Hydrochloride Tablets are available in three strengths as follows:
100 mg, Mottled pink, round, flat-faced, bevelled-edge tablets, engraved “^
53” on one side and plain on other side.
Blistercards of 30 NDC 0615-8607-39

200 mg, Mottled pink, round, flat-faced, bevelled-edge tablets, engraved ‘^’ over score and ‘54’ below score on one side and plain on other side
400 mg, Mottled pink, round, flat-faced bevelled-edge tablets, engraved “^” over score and “055” below score on one side and plain on the other side.

Store at 20°C to 25°C (68°F to 77°F) excursions permitted from 15°C to 30°C (59°F to 86°F) [see USP Controlled Room Temperature].

Protect from light.

Dispense in a tight, light-resistant container [See USP].

17 PATIENT COUNSELING INFORMATION

Advise the patient to read the FDA-approved patient labeling (Medication Guide).

Advise pregnant women of the potential risk to a fetus. Advise females of reproductive potential to inform their prescriber of a known or suspected pregnancy [see Use in Specific Populations (8.1)].

Advise women that breastfeeding is not recommended during treatment with Amiodarone Hydrochloride Tablets [see Use in Specific Populations (8.2)].

Advise patients to avoid grapefruit juice and St. John's Wort.

Advise patients to seek medical attention if they experience the signs and symptoms of pulmonary toxicity, worsening arrhythmia, bradycardia, visual impairment, or hypo- and hyperthyroidism.

Manufactured by Distributed by:
Rubicon Research Ltd., Advagen Pharma Ltd.,
Thane 421506, India East Windsor, NJ 08520, USA

MEDICATION GUIDE
Amiodarone Hydrochloride Tablets
(A-mee-OH-da-rone)

What is the most important information I should know about Amiodarone Hydrochloride Tablets? Amiodarone

Hydrochloride tablets can cause serious side effects that can lead to death, including:

- lung problems
- liver problems
- worsening of heartbeat problems

Call your healthcare provider or get medical help right away if you have any of the following symptoms during treatment with Amiodarone Hydrochloride Tablets:

- trouble breathing, wheezing, shortness of breath, coughing chest pain, spitting up of blood, or fever
- nausea or vomiting, brown or dark-colored urine, feel more tired than usual, yellowing of your skin or the whites of your eyes (jaundice), or right upper stomach-area pain
- heart pounding, skipping a beat, beating fast or slowly, feel light-headed, or if you faint
- vision problems, including blurred vision, see halos, or your eyes become sensitive to light. You should have regular eye exams before and during treatment with Amiodarone Hydrochloride Tablets.

Amiodarone Hydrochloride Tablets should be started in a hospital so that your medical condition can be carefully monitored. Amiodarone Hydrochloride Tablets should only be used to treat people who have been diagnosed with life-threatening heartbeat problems called ventricular arrhythmias, when other treatments did not work or you cannot tolerate them.

Amiodarone Hydrochloride Tablets can cause other serious side effects. See “What are the possible side effects of Amiodarone Hydrochloride Tablets?” If you get serious side effects during treatment you may need to stop Amiodarone Hydrochloride Tablets, have your dose changed, or get medical treatment. Talk with your healthcare provider before you stop taking Amiodarone Hydrochloride Tablets.

You may still have side effects after stopping Amiodarone Hydrochloride Tablets because the medicine stays in your body for months after treatment is stopped.

You should have regular check-ups, blood tests, chest x-rays before and during treatment with Amiodarone Hydrochloride Tablets to check for serious side effects. You should also have lung function tests before starting treatment with Amiodarone Hydrochloride Tablets.

What is Amiodarone Hydrochloride Tablets?

Amiodarone Hydrochloride Tablets is a prescription medicine used to treat people who have been diagnosed with life-threatening heartbeat problems called ventricular arrhythmias, when other treatments did not work or you cannot tolerate them.

It is not known if Amiodarone Hydrochloride Tablets is safe and effective in children.

Who should not take Amiodarone Hydrochloride Tablets? Do not take Amiodarone Hydrochloride Tablets if you:

- have a serious heart problem called cardiogenic shock
- have certain types of the heart condition called heart block, with or without a slow heart rate
- have a slow heart rate with dizziness or lightheadedness, and you do not have an implanted pacemaker
- are allergic to amiodarone, iodine, or any of the other ingredients in Amiodarone Hydrochloride Tablets. See the end of this Medication Guide for a complete list of ingredients in Amiodarone Hydrochloride Tablets.

Before taking Amiodarone Hydrochloride Tablets, tell your healthcare provider about all of your medical conditions, including if you:

- have lung or breathing problems
- have liver problems
- have or had thyroid problems
- have a slow heart rate or blood pressure problems
- have diarrhea or have had diarrhea for a long period of time
- have been told that you have low levels of potassium, magnesium, or calcium in your blood
- have an implanted pacemaker or defribrillator
- if you plan to have surgery with general anesthesia
- are pregnant or plan to become pregnant. Amiodarone Hydrochloride Tablets may harm your unborn baby. Tell your healthcare provider right away if you become pregnant during treatment with Amiodarone Hydrochloride Tablets. Amiodarone Hydrochloride Tablets can stay in your body for months after treatment is stopped.
- are breastfeeding or plan to breastfeed. Amiodarone Hydrochloride Tablets can pass into your breast milk and may harm your baby.
- You should not breast feed while taking Amiodarone Hydrochloride Tablets. Amiodarone Hydrochloride Tablets can stay in your body for months after treatment is stopped. Talk to your healthcare provider about the best way to feed your baby during this time.

Tell your healthcare provider about all the medicines you take including prescription and over-the-counter medicines, vitamins, and herbal supplements. Amiodarone Hydrochloride Tablets and certain other medicines can affect with each other and cause serious side effects. You can ask your pharmacist for a list of medicines that interact with Amiodarone Hydrochloride Tablets.

How should I take Amiodarone Hydrochloride Tablets?

- When you are discharged from the hospital, take Amiodarone Hydrochloride Tablets exactly as your doctor tells you to take it.
- Your healthcare provider will tell you how much Amiodarone Hydrochloride Tablets to take and when to take it.
- Your healthcare provider may change your dose of Amiodarone Hydrochloride Tablets as needed if your heart rhythm is controlled, or if you have certain side effects. Your healthcare provider should monitor you carefully when your dose of Amiodarone Hydrochloride Tablets is being changed.
- Take your dose of Amiodarone Hydrochloride Tablets the same way each time, either with or without food.
- If you take too much Amiodarone Hydrochloride Tablets, call your healthcare provider or go to the nearest hospital emergency room right away. If you miss a dose, wait and take your next dose at your regular time. Do not take two doses at the same. Continue with your next regularly scheduled dose.

What should I avoid while taking Amiodarone Hydrochloride Tablets?

- Avoid drinking grapefruit juice during treatment with Amiodarone Hydrochloride Tablets. Drinking grapefruit juice with Amiodarone Hydrochloride Tablets may increase the amount of Amiodarone Hydrochloride Tablets in your blood, and this may lead to side effects.
- Amiodarone Hydrochloride Tablets can make your skin sensitive to sunlight. You could get severe sunburn. Use sunscreen and wear a hat and clothes that cover your skin to help protect you if you must be in sunlight. Talk to your healthcare if you get a sunburn. See “Skin problems” in the Medication Guide section “What are the possible side effects of Amiodarone Hydrochloride Tablets?”below.

What are the possible side effects of Amiodarone Hydrochloride Tablets? Amiodarone Hydrochloride Tablets can cause serious side effects, including:

- See “What is the most important information I should know about Amiodarone Hydrochloride Tablets?”
- Nerve problems.Amiodarone Hydrochloride Tablets can cause nerve problems. Call your healthcare provider if you develop symptoms of nerve problems, including: a feeling of “pins and needles” or numbness in your hands, legs, or feet, muscle weakness, uncontrolled movements, poor coordination, or trouble walking.
- Skin problems.Amiodarone Hydrochloride Tablets can cause your skin to be more sensitive to the sun or turn a bluish-gray color. People who have fair skin or people who have a lot of sun exposure may be more at risk for these skin problems. Some of the bluish-gray skin color may return to normal after stopping Amiodarone Hydrochloride Tablets.
- Thyroid problems.Amiodarone Hydrochloride Tablets can cause you to have either decreased thyroid function (hypothyroidism), which can sometimes be severe, or an overactive thyroid (hyperthyroidism), which can be severe.
  - If you develop decreased thyroid function during treatment with Amiodarone Hydrochloride Tablets, your healthcare provider may need to reduce your dose or stop your treatment with Amiodarone Hydrochloride Tablets, and possibly prescribe medicine to replace your thyroid hormone.
  - An overactive thyroid can cause you to produce too much thyroid hormone. You can have abnormal heartbeats even while you are receiving Amiodarone Hydrochloride Tablets. Your healthcare provider may prescribe certain medicines to treat your overactive thyroid. Call your healthcare provider if you get any abnormal heart beats during treatment with Amiodarone Hydrochloride Tablets. This may mean that you have an overactive thyroid.
  - Your healthcare provider should do tests to check your thyroid function before you start and during treatment with Amiodarone Hydrochloride Tablets.
  - Call your healthcare provider if you develop any of the following symptoms of a thyroid problem during treatment with Amiodarone Hydrochloride Tablets:

■ weakness ■ nervousness
■ weight loss or weight gain ■ irritability
■ heat or cold intolerance ■ restlessness
■ hair thinning ■ decreased concentration
■ sweating ■ feeling depressed (in the elderly)
■ changes in your menstrual periods ■ tremor
■ swelling of your neck (goiter)

The most common side effects of Amiodarone Hydrochloride Tablets include:

- lung problems
- heartbeat problems
- heart problems
- liver problems

Amiodarone Hydrochloride Tablets may affect fertility in males and females. It is not known if the effects are reversible. Talk to your healthcare provider if you have concerns about fertility.

These are not all the possible side effects of Amiodarone Hydrochloride Tablets. For more information, ask your healthcare provider or pharmacist.

Call your doctor for medical advice about side effects. You may report side effects to FDA at 1-800-FDA-1088.

How should I store Amiodarone Hydrochloride Tablets?

- Store Amiodarone Hydrochloride Tablets at room temperature between 20° to 25°C (68° to 77°F).
- Keep Amiodarone Hydrochloride Tablets in a tightly closed container, and keep Amiodarone Hydrochloride Tablets out of the light.

Keep Amiodarone Hydrochloride Tablets and all medicines out of the reach of children.

General information about the safe and effective use of Amiodarone Hydrochloride Tablets

Medicines are sometimes prescribed for purposes other than those listed in a Medication Guide. Do not use Amiodarone Hydrochloride Tablets for a condition for which it was not prescribed. Do not give Amiodarone Hydrochloride Tablets to other people, even if they have the same symptoms that you have. It may harm them. You can ask your pharmacist or healthcare provider for information about Amiodarone Hydrochloride Tablets that is written for health professionals.

What are the ingredients in Amiodarone Hydrochloride Tablets? Active Ingredient: amiodarone HCl

Inactive Ingredients:colloidal silicon dioxide, croscarmellose sodium, crospovidone, FD&C Red #40 Al Lake and magnesium stearate.

All brand names are the trademarks of their respective owners.

Manufactured by Distributed by:
Rubicon Research Ltd., Advagen Pharma Ltd.,
Thane 421506, India East Windsor, NJ 08520, USA

For more information, go to www.advagenpharma.comor call 866-488-0312

This Medication Guide has been approved by the U.S. Food and Drug Administration. Rev.02, 11/2024